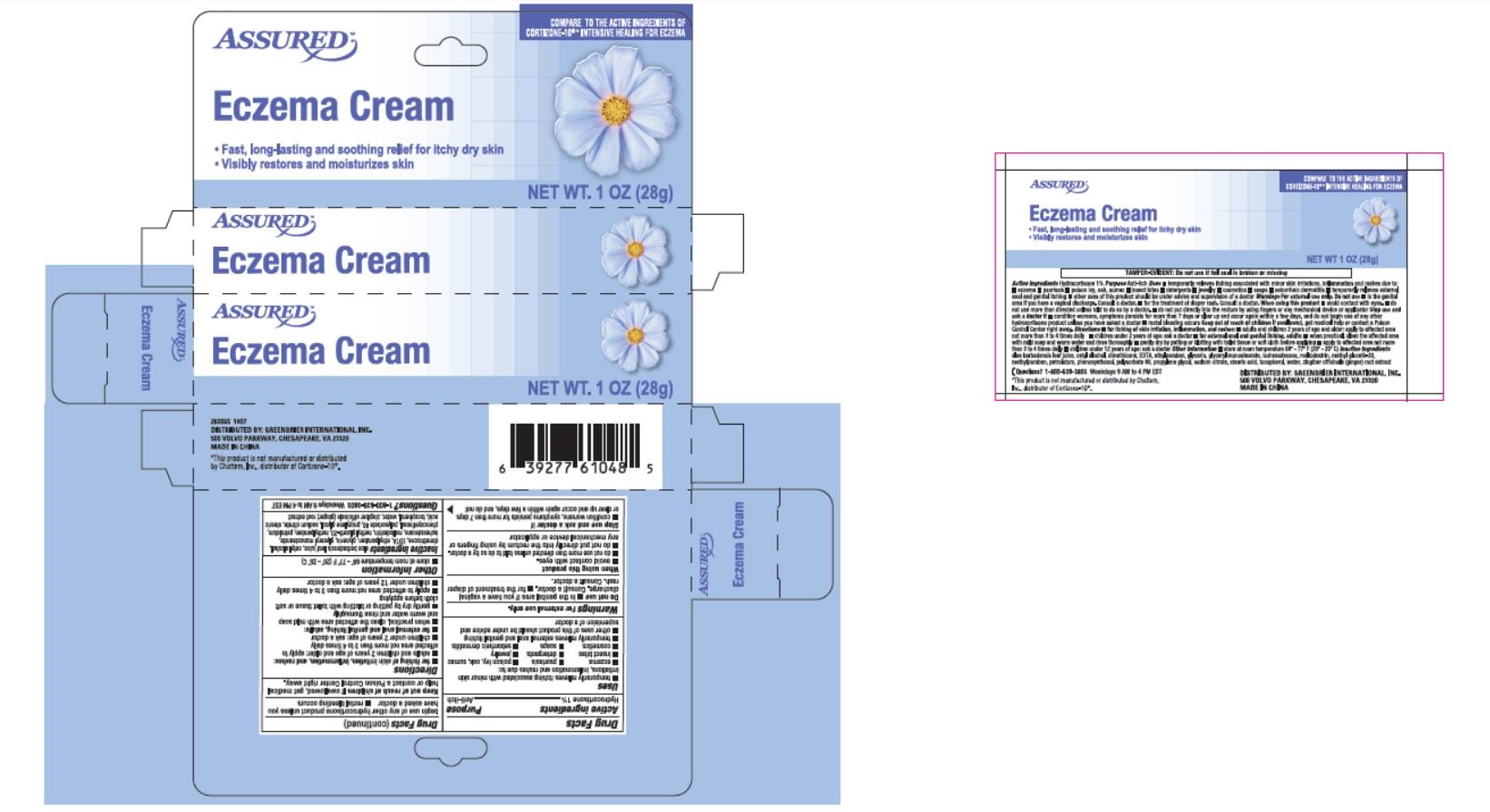 DRUG LABEL: Assured
NDC: 55621-018 | Form: CREAM
Manufacturer: Zhejiang Jingwei Pharmaceutic Al Co., Ltd.
Category: otc | Type: HUMAN OTC DRUG LABEL
Date: 20231025

ACTIVE INGREDIENTS: HYDROCORTISONE 1 g/100 g
INACTIVE INGREDIENTS: ALOE VERA LEAF; CETYL ALCOHOL; DIMETHICONE; EDETIC ACID; ETHYLPARABEN; GLYCERIN; GLYCERYL MONOSTEARATE; ISOHEXADECANE; MALTODEXTRIN; METHYL GLUCETH-20; METHYLPARABEN; PETROLATUM; PHENOXYETHANOL; POLYSORBATE 80; PROPYLENE GLYCOL; SODIUM CITRATE; STEARIC ACID; TOCOPHEROL; WATER; GINGER

Active ingredients

Hydrocortisone 1%

Purpose

Anti-itch

Uses

•temporarily relieves itching ssociated with minor skin

irritation, inflammation and rashesdue to:

•eczema •psoriasis •poison ivy, oak, sumac

•insect bites •detergents •jewelry

•cosmetics •soaps •seborrheic dermatitis

•temporarily relieves external anal and genital itching

•other uses of this product should be under advice and

supervision of a doctor

. Warnings. For external use only

•in the genital area if you have a vaginal Do not use

discharge. Consult a doctor •for the treatment of diaper

rash. Consult a doctor.

When using this product

•avoid contact with eyes.

•do not use more than directed unless told to do so by a doctor.

•do not put directly into rectum by using fingers or

any mechanical device or applicator.

Stop use and ask a doctor if

•condition worsens, symptoms persist for more than 7 days

or clear up and occur again within a few days, and do not

begin use of any other hydrocortisone product unless you

have asked a doctor. •rectal bleeding occurs.

KEEP OUT OF REACH OF CHILDREN

. If swallowed, get medical Keep out of reach of children

help or contract a Poison Control Center right away.

Directions

• : for relieving of skin irritation, inflammation, and rashes

•adults and children 2 years of age and older: apply to

affected area not more than 3 to 4 times daily

•children under 2 years of age: ask a doctor

• s: for external anal and genital itching, adult

•when practical, clean the affected area with mild soap

and warm water and rinse thoroughly

•gently dry by patting or blotting with toilet tissue or soft

cloth before applying

•apply to affected area not more than 3 to 4 times daily

•children under 12 years of age: ask a doctor

Other information

•store at room temperature 68° - 77° F (20° - 25° C)

aloe barbadensis leaf juice, cetyl alcohol, Inactive ingredients

dimethicone, EDTA, ethylparaben, glycerin, glyceryl monostearate,

isohexadecane, maltodextrin, methyl gluceth-20, methyparaben, petrolatum,

phenoxyethanol, polysorbate 80, propylene glycol, sodium citrate, stearic

acid, tocopherol, water, zingiber officinale (ginger) root extract

QUESTIONS

1-800-639-3803 Weekdays 9 AM to 4 PM EST Questions?